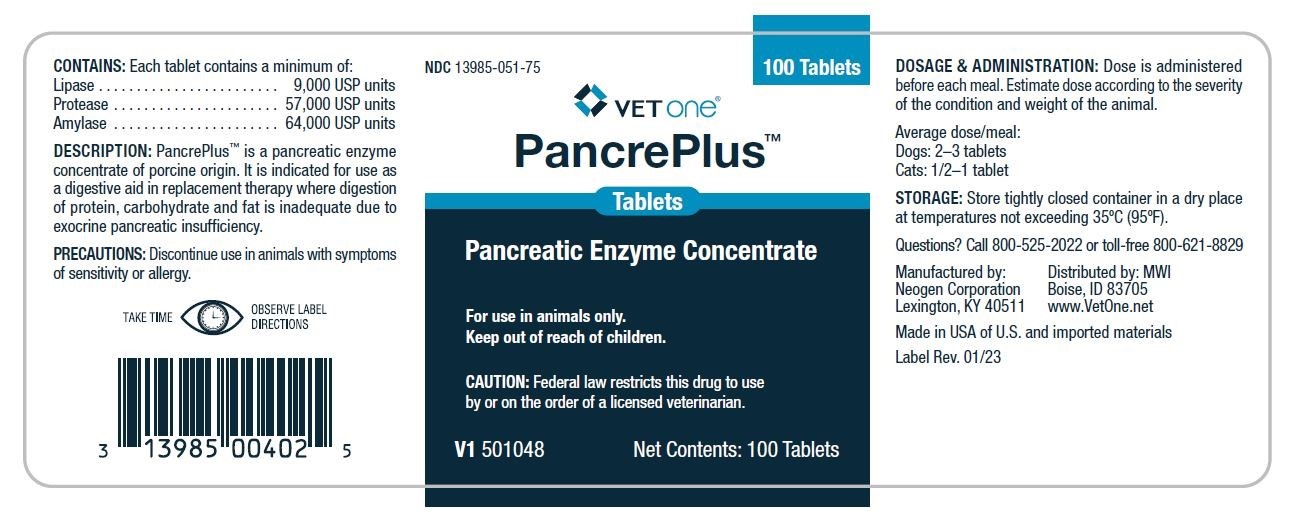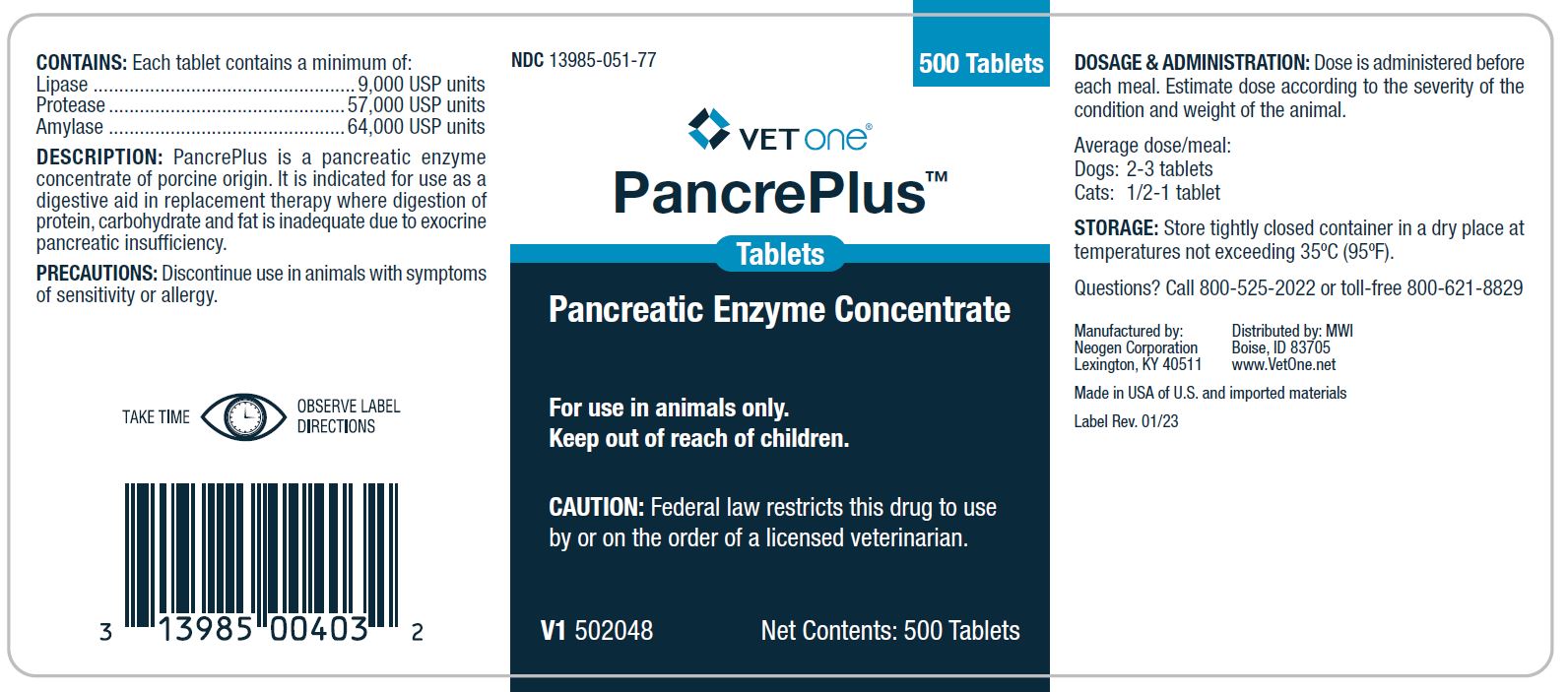 DRUG LABEL: PancrePlus
NDC: 13985-051 | Form: TABLET
Manufacturer: MWI/VetOne
Category: animal | Type: PRESCRIPTION ANIMAL DRUG LABEL
Date: 20231213

ACTIVE INGREDIENTS: PANCRELIPASE LIPASE 9000 [iU]/1 1; PANCRELIPASE PROTEASE 57000 [iU]/1 1; PANCRELIPASE AMYLASE 64000 [iU]/1 1

DESCRIPTION

PancrePlus

Tablets

Pancreatic Enzyme Concentrate

For use in animals only.

Keep out of reach of children.

CAUTION: Federal law restricts this drug to use by or on the order of a licensed veterinarian.

CONTAINS: Each tablet contains a minimum of:

Lipase........................................9,000 USP units

Protease...................................57,000 USP units

Amylase....................................64,000 USP units

DESCRIPTION:

PancrePlusis a pancreatic enzyme concentrate of porcine origin. It is indicated for use as a digestive aid in replacement therapy where digestion of protein, carbohydrate and fat is inadequate due to exocrine pancreatic insufficiency.

PRECAUTIONS:

Discontinue use in animals with symptoms of sensitivity or allergy.

MADE IN USA of U/S. and imported materials

DOSAGE & ADMINISTRATION:

Dose is administered before each meal. Estimate dose according to the severity of the condition and weight of the animal.

Average Dose/meal:

Dogs: 2-3 tablets

Cats: 1/2-1 tablet

STORAGE:

Store tightly closed container in a dry place at temperatures not exceeding 35°C (95°F).

WARNINGS

TAKE TIME

OBSERVE LABEL DIRECTIONS

Questions? Call 800-525-2022 or toll-free 800-621-8829

Distributed by: MWI

Boise, ID 83705

www.VetOne.net

Manufactured by:

Neogen Corporation

Lexington, KY 40511

PRINCIPAL DISPLAY PANEL PancrePlus Tablets 100 Tablet Bottle

NDC 13985-051-75

100 Tablets

VETone®

PancrePlus

Tablets

Pancreatic Enzyme Concentrate

For use in animals only.

Keep out of reach of children.

CAUTION: Federal law restricts this drug to use by or on the order of a licensed veterinarian.

V1 501048 Net Contents: 100 Tablets

PRINCIPAL DISPLAY PANEL PancrePlus Tablets 500 Tablet Bottle

NDC 13985-051-77

500 Tablets

VETone®

PancrePlus

Tablets

Pancreatic Enzyme Concentrate

For use in animals only.

Keep out of reach of children.

CAUTION: Federal law restricts this drug to use by or on the order of a licensed veterinarian.

V1 502048 Net Contents: 500 Tablets